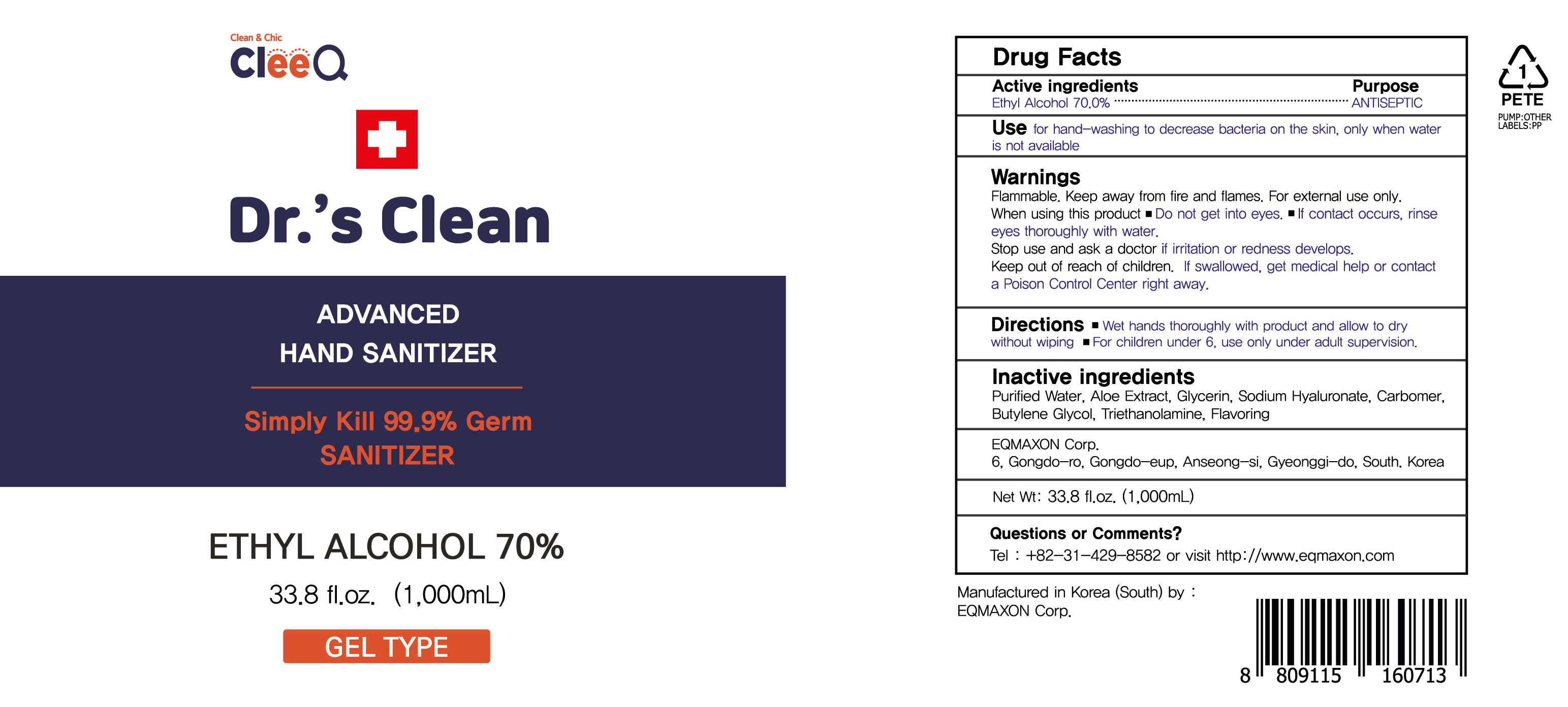 DRUG LABEL: Dr.s Clean Advanced Hand Sanitizer
NDC: 55526-0017 | Form: GEL
Manufacturer: EQMAXON Corp.
Category: otc | Type: HUMAN OTC DRUG LABEL
Date: 20210629

ACTIVE INGREDIENTS: ALCOHOL 700 mL/1000 mL
INACTIVE INGREDIENTS: Water; ALOE; Glycerin; HYALURONATE SODIUM; CARBOMER HOMOPOLYMER, UNSPECIFIED TYPE; Butylene Glycol; TROLAMINE

ACTIVE INGREDIENT

Ethyl Alcohol 70.0%

INACTIVE INGREDIENTS

Purified Water, Aloe Extract, Glycerin, Sodium Hyaluronate, Carbomer, Butylene Glycol, Triethanolamine, Flavoring

PURPOSE

ANTISEPTIC

WARNINGS

Flammable. Keep away from fire and flames. For external use only.

When using this product • Do not get into eyes. • If contact occurs, rinse eyes thoroughly with water.

Stop use and ask a doctor if irritation or redness develops.

Keep out of reach of children. If swallowed, get medical help or contact a Poison Control Center right away

Keep out of reach of children. If swallowed, get medical help or contact a Poison Control Center right away

Uses

for hand-washing to decrease bacteria on the skin, only when water is not available

Directions

Wet hands thoroughly with product and allow to dry without wiping

For children under 6, use only under adult supervision.

Questions

+82-31-429-8582 or visit http://www.eqmaxon.com